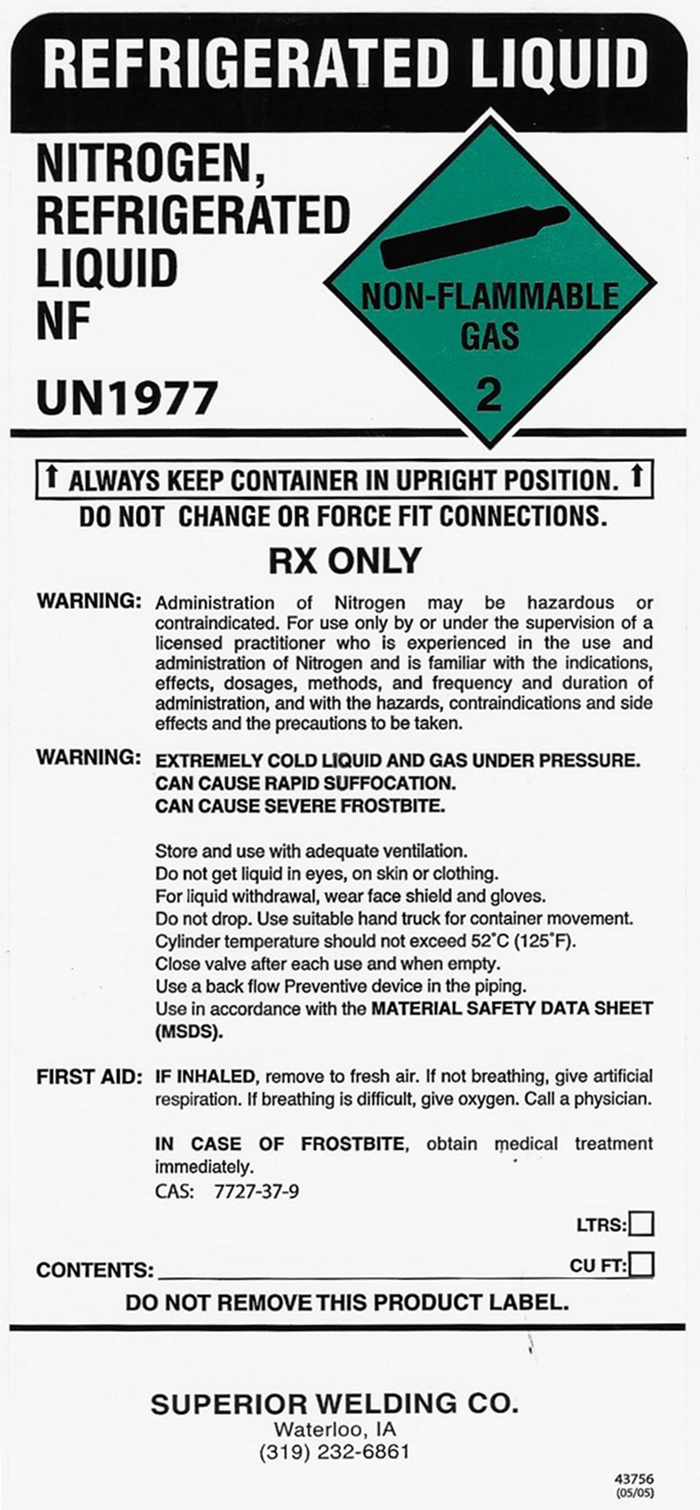 DRUG LABEL: NITROGEN
NDC: 49653-002 | Form: GAS
Manufacturer: Superior Welding Supply Co
Category: prescription | Type: HUMAN PRESCRIPTION DRUG LABEL
Date: 20251114

ACTIVE INGREDIENTS: NITROGEN 990 mL/1 L

Nitrogen

NITROGEN REFRIGERATED LIQUID LABEL

NITROGEN, REFRIGERATED LIQUID NF UN1977 NON-FLAMMABLE GAS 2

↑ALWAYS KEEP CONTAINER IN UPRIGHT POSITION. ↑

DO NOT CHANGE OR FORCE FIT CONNECTIONS.

RX ONLY

WARNING: Administration of Nitrogen may be hazardous or contraindicated. For use only by or under the supervision of a licensed practitioner who is experienced in the use and administration of Nitrogen and is familiar with the indications, effects, dosages, methods, and frequency and duration of administration, and with the hazards, contraindications and side effects and the precautions to be taken.

WARNING: EXTREMELY COLD LIQUID AND GAS UNDER PRESSURE. CAN CAUSE RAPID SUFFOCATION. CAN CAUSE SEVERE FROSTBITE.

Store and use with adequate ventilation. Do not get liquid in eyes, on skin or clothing. For liquid withdrawal, wear face shield and gloves. Do not drop. Use suitable hand truck for container movement. Cylinder temperature should not exceed 52°C (125°F). close valve after each use and when empty. Use a back flow Preventive device in the piping. Use in accordance with the MATERIAL SAFETY DATA SHEET (MSDS).

FIRST AID: IF INHALED, remove to fresh air. If not breathing, give artificial respiration. If breathing is difficult, give oxygen. Call a physician.

IN CASE OF FROSTBITE, obtain medical treatment immediately.

CAS: 7727-37-9

CONTENTS: ___________________________________ LTRS: ___ CU FT: ___

DO NOT REMOVE THIS PRODUCT LABEL.

SUPERIOR WELDING CO.

Waterloo, IA

(319)232-6861

43756 (05/05)